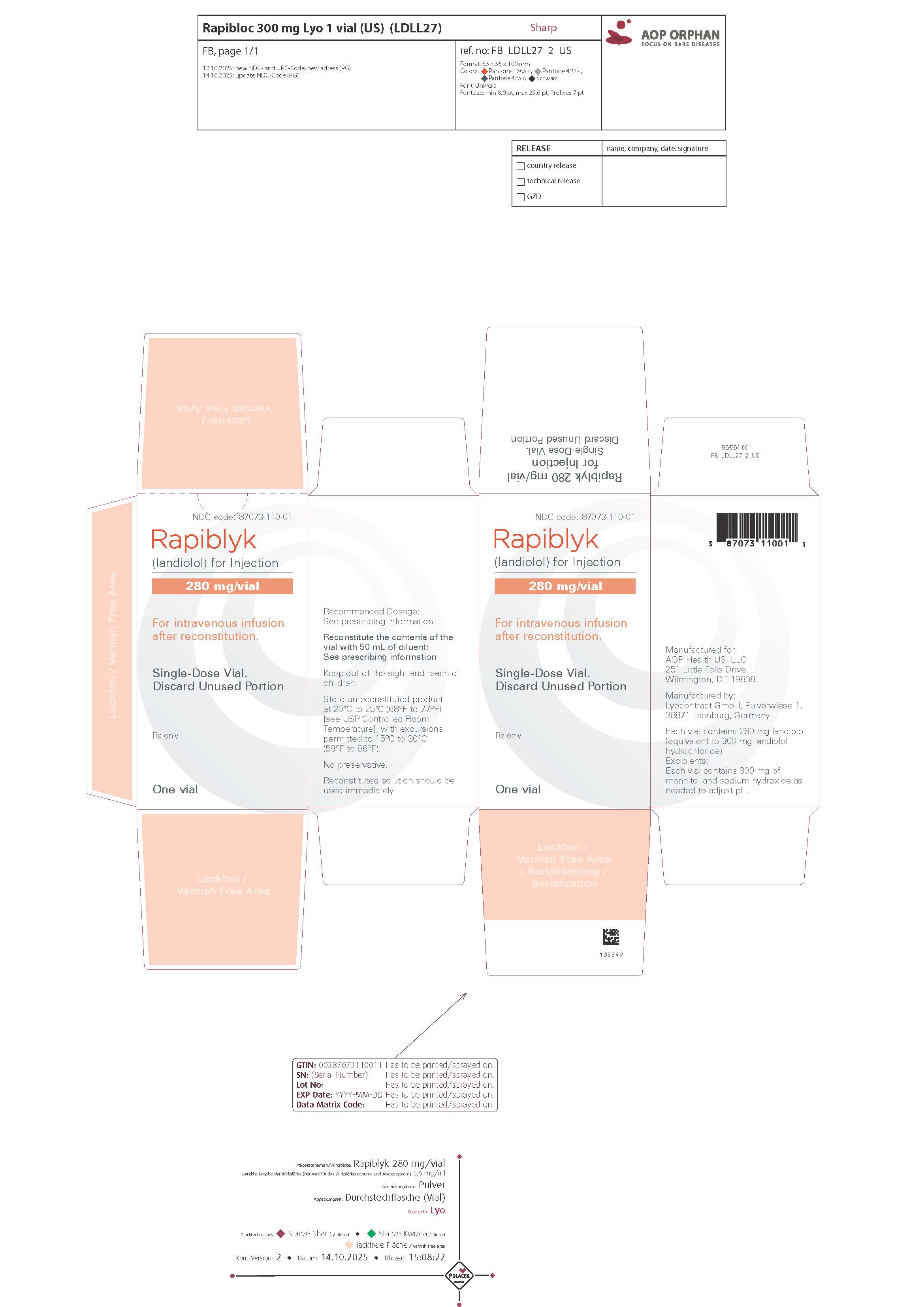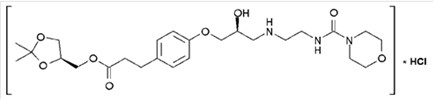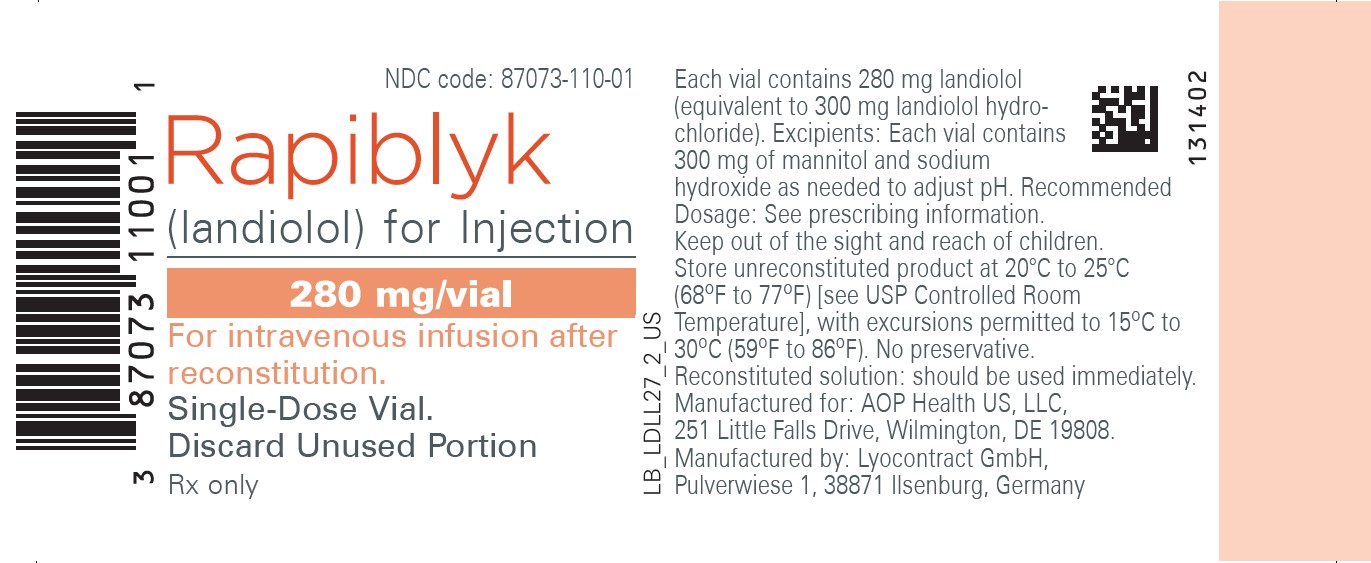 DRUG LABEL: RAPIBLYK
NDC: 87073-110 | Form: INJECTION, POWDER, LYOPHILIZED, FOR SOLUTION
Manufacturer: AOP Health US, LLC
Category: prescription | Type: HUMAN PRESCRIPTION DRUG LABEL
Date: 20260213

ACTIVE INGREDIENTS: LANDIOLOL HYDROCHLORIDE 280 mg/1 1
INACTIVE INGREDIENTS: SODIUM HYDROXIDE; MANNITOL 300 mg/1 1

HIGHLIGHTS OF PRESCRIBING INFORMATION

These highlights do not include all the information needed to use RAPIBLYK® safely and effectively. See full prescribing information for RAPIBLYK.
RAPIBLYK (landiolol) for injection, for intravenous use
Initial U.S. Approval: 2024

1 INDICATIONS AND USAGE

RAPIBLYK is a beta adrenergic blocker indicated for the short-term reduction of ventricular rate in:

- adults with supraventricular tachycardia including atrial fibrillation and atrial flutter (1), and
- pediatric patients with supraventricular tachycardia. (1)

2 DOSAGE AND ADMINISTRATION

- Administer as an intravenous infusion in a monitored setting. (2.1)
- Titrate according to ventricular rate. (2.1)
- In adults with normal cardiac function, start at 9 mcg/kg/min; adjust dose in 10-minute intervals as needed in increments of 9 mcg/kg/min to a maximum of 36 mcg/kg/min. (2.1)
- In adults with If impaired cardiac function, start at 1 mcg/kg/min; adjust dose in 15-minute intervals as needed in increments of 1 mcg/kg/min to a maximum of 36 mcg/kg/min. (2.1)
- In pediatric patients, start at 9 mcg/kg/min; adjust dose in 10-minute intervals as needed in increments of 9 mcg/kg/min to a maximum of 36 mcg/kg/min. (2.1)

3 DOSAGE FORMS AND STRENGTHS

For injection: 280 mg of landiolol (equivalent to 300 mg of landiolol HCl) as a lyophilized powder in a single-dose vial. (3)

4 CONTRAINDICATIONS

- 5.3Severe sinus bradycardia (4)
- Sick sinus syndrome (4)
- Heart block greater than first degree (4)
- Decompensated heart failure (4)
- Cardiogenic shock (4)
- Pulmonary hypertension (4)
- Known hypersensitivity to landiolol (4)

5 WARNINGS AND PRECAUTIONS

- Risk of hypotension, bradycardia, and cardiac failure: Monitor for signs and symptoms of cardiovascular adverse effects. Reduce or discontinue use (5.1, 5.2, 5.3)
- Risk of exacerbating reactive airway disease (5.5)
- Diabetes mellitus: May mask symptoms of hypoglycemia and alter glucose levels; monitor (5.6)
- Monitor for signs of myocardial ischemia when abruptly discontinuing in patients with coronary artery disease (5.10)

6 ADVERSE REACTIONS

The most common adverse reaction (9.9%) is hypotension (6.1).

To report SUSPECTED ADVERSE REACTIONS, contact AOP Orphan Pharmaceuticals at drugsafety.us@aop-health.com or FDA at 1-800-FDA-1088 or www.fda.gov/medwatch.

7 DRUG INTERACTIONS

- Negative Inotropes and Chronotropes: Avoid (7.1)
- Sympathomimetics, Positive Inotropes and Vasoconstrictors: Avoid (7.2)
- Catecholamine Depleting Drugs: Monitor blood pressure and heart rate (7.3).

17. Recent Major Changes

Below section were updated with pediatric patients

• Indications and Usage (1)
• Dosage and Administration (2.1)

FULL PRESCRIBING INFORMATION

1 INDICATIONS AND USAGE

RAPIBLYK is indicated for the short-term reduction of ventricular rate in

- adults with supraventricular tachycardia including atrial fibrillation and atrial flutter, and
- pediatric patients with supraventricular tachycardia.

2 DOSAGE AND ADMINISTRATION

2.1 Recommended Dosage

Administer RAPIBLYK as a continuous intravenous infusion in a monitored setting, titrating as needed for heart rate control. There are limited data beyond 24 hours of use.

 | Adults |  | Pediatric patients
 | Normal cardiac function | Impaired cardiac function | Normal cardiac function*
Starting dose | 9 mcg/kg/min | 1 mcg/kg/min | 9 mcg kg/min
Titration interval | 10 min | 15 min | 10 min
Titration step | 9 mcg/kg/min | 1 mcg/kg/min | 9 mcg kg/min
Maximum dose | 36 mcg/kg/min | 36 mcg/kg/min | 36 mcg kg/min

*There are no data to guide dosage recommendations in pediatric patients with impaired cardiac function.

2.2 Transitioning from RAPIBLYK Injection Therapy to Alternative Medications

When transitioning to alternative medications consider the pharmacodynamics of the medication to which the patient is being transitioned and monitor clinical response. If switched to an oral beta-blocker, the dosage of RAPIBLYK can be reduced as follows:

- Ten minutes after administration of the oral beta-blocker, reduce the infusion rate of RAPIBLYK by 50%.
- If satisfactory control is maintained for at least one hour, discontinue RAPIBLYK.

2.3 Instructions for Preparation

- Use appropriate aseptic technique for reconstitution.
- Reconstitute each 280 mg vial of RAPIBLYK with 50 mL of 0.9% Sodium Chloride Injection, USP or 5% Dextrose Injection, USP. Gently swirl to dissolve contents.
- Inspect parenteral drug products for particulate matter and discoloration prior to administration, whenever solution and container permit. The reconstituted solution should be a clear, colorless solution.
- Use immediately. The reconstituted RAPIBLYK solution storage conditions are described in Table 2.
- Discard unused portion.

Table 2: Reconstituted RAPIBLYK Solution Storage and Use Conditions
Diluent used to Prepare Solution | Reconstituted RAPIBLYK Solution Storage and Use Conditions
50 mL of 0.9% Sodium Chloride Injection, USP | Use within 4 hours at room temperature (25°C, 77°F)
50 mL of 5% Dextrose Injection, USP | Use within 48 hours at room temperature (25°C, 77°F)

2.4 Administration

Following reconstitution, the product contains 280 mg landiolol/50 mL = 5.6 mg/mL.

The infusion rate can be calculated as:

- Infusion rate (mL/hour) = target dose (mcg/kg/min) × body weight (kg) / 93

3 DOSAGE FORMS AND STRENGTHS

For injection: White to almost white lyophilized powder in a single-dose vial containing 280 mg of landiolol (equivalent to 300 mg landiolol HCl).

4 CONTRAINDICATIONS

RAPIBLYK is contraindicated in patients with:

- Severe sinus bradycardia, sick sinus syndrome, heart block greater than first degree [see Warnings and Precautions (5.2)].
- Decompensated heart failure [see Warnings and Precautions (5.3)].
- Cardiogenic shock: May precipitate further cardiovascular collapse and cause cardiac arrest.
- Pulmonary hypertension: May precipitate cardiorespiratory decompensation.
- Hypersensitivity reactions, including anaphylaxis, to landiolol or any of the inactive ingredients

5 WARNINGS AND PRECAUTIONS

5.1 Hypotension

Patients with hemodynamic compromise, hypovolemia, or on interacting medications are at increased risk of hypotension. Monitor blood pressure closely, especially if pretreatment blood pressure is low. Reduce or stop RAPIBLYK injection for hypotension then expect the blood pressure effect to wane within 30 minutes.

5.2 Bradycardia

Patients with first-degree atrioventricular block, sinus node dysfunction, or conduction disorders are at increased risk of bradycardia, including sinus pause, heart block, severe bradycardia, and cardiac arrest. Monitor heart rate and rhythm in patients receiving RAPIBLYK injection. Reduce or stop RAPIBLYK injection for bradyarrhythmia.

5.3 Cardiac Failure

Beta-blockers, like RAPIBLYK, can cause depression of myocardial contractility and may precipitate heart failure and cardiogenic shock. At the first sign or symptom of impending cardiac failure, stop RAPIBLYK injection and start supportive therapy [see Overdosage (10)].

5.4 Reactive Airways Disease

Patients with reactive airways disease should, in general, not receive beta-blockers. Because of its relative beta-1 selectivity and titratability, RAPIBLYK injection may be titrated to the lowest possible effective dose. In the event of bronchospasm, stop the infusion immediately; a beta-2 stimulating agent may be administered with appropriate monitoring of ventricular rates.

5.5 Use in Patients with Diabetes Mellitus and Hypoglycemia

Beta-blockers may prevent early warning signs of hypoglycemia, such as tachycardia, and increase the risk for severe or prolonged hypoglycemia at any time during treatment, especially in patients with diabetes mellitus, patients who are fasting (i.e., surgery, not eating regularly, or are vomiting), or pediatric patients. Monitor for signs and symptoms of hypoglycemia in patients receiving RAPIBLYK.

5.6 Infusion Site Reactions

Infusion site reactions such as pain, swelling and erythema have occurred with the use of RAPIBLYK injection. Avoid infusions into small veins or through a butterfly catheter. If a local infusion site reaction develops, use an alternative infusion site and avoid extravasation.

5.7 Use in Patients with Prinzmetal’s Angina

Beta-blockers may exacerbate anginal attacks in patients with Prinzmetal’s angina because of unopposed alpha receptor–mediated coronary artery vasoconstriction.

5.8 Use in Patients with Pheochromocytoma

If RAPIBLYK injection is used in the setting of pheochromocytoma, administer RAPIBLYK in combination with an alpha-blocker, and only after the alpha-blocker has been initiated. Administration of beta-blockers without opposing alpha blockade in the setting of pheochromocytoma has been associated with a paradoxical increase in blood pressure from the attenuation of beta receptor-mediated vasodilation in skeletal muscle.

5.9 Use in Patients with Peripheral Circulatory Disorders

RAPIBLYK injection may exacerbate peripheral circulatory disorders, such as Raynaud’s disease or syndrome, and peripheral occlusive vascular disease.

5.10 Abrupt Discontinuation of RAPIBLYK Injection

Severe exacerbations of angina, myocardial infarction, and ventricular arrhythmias have been reported in patients with coronary artery disease upon abrupt discontinuation of beta-blocker therapy. Observe patients for signs of myocardial ischemia when discontinuing RAPIBLYK injection.

5.11 Hyperkalemia

Beta-blockers, including RAPIBLYK injection, can cause increases in serum potassium and hyperkalemia. The risk is increased in patients with risk factors such as renal impairment. Intravenous administration of beta-blockers has been reported to cause potentially life-threatening hyperkalemia in hemodialysis patients. Monitor serum electrolytes during therapy with RAPIBLYK injection.

5.12 Use in Patients with Metabolic Acidosis

Beta-blockers have been reported to cause hyperkalemic renal tubular acidosis. Acidosis in general may be associated with reduced cardiac contractility.

5.13 Use in Patients with Hyperthyroidism

Beta-adrenergic blockade may mask certain clinical signs (e.g., tachycardia) of hyperthyroidism. Abrupt withdrawal of beta blockade might precipitate thyroid storm; therefore, monitor patients for signs of thyrotoxicosis when withdrawing beta blocking therapy.

5.14 Use in Patients at Risk of Severe Acute Hypersensitivity Reactions

When using beta-blockers, patients at risk of anaphylactic reactions may be more reactive to allergen exposure (accidental, diagnostic, or therapeutic).

Patients using beta-blockers may be unresponsive to the usual doses of epinephrine used to treat anaphylactic or anaphylactoid reactions [see Drug Interactions (7)].

6 ADVERSE REACTIONS

6.1 Clinical Trials Experience

Because clinical trials are conducted under widely varying conditions, the adverse reaction rates observed in the clinical trials of a drug cannot be directly compared to rates in the clinical trials of another drug and may not reflect the rates observed in clinical practice.

The safety of RAPIBLYK was evaluated in 19 placebo-controlled clinical trials involving 1,761 adult patients (in a variety of clinical in-patient settings) with supraventricular tachycardia or at high risk for supraventricular tachycardia. The most common adverse reaction is hypotension, which occurred in 9.9% of patients receiving RAPIBLYK vs. 1% in those receiving placebo [see Warnings and Precautions (5.1)].

In a single-arm, unblinded clinical trial in 60 pediatric patients who received RAPIBLYK, the most common adverse reaction was hypotension, which occurred in 10% of patients aged birth to <18 years receiving RAPIBLYK [see Warnings and Precautions (5.1)]. Hypotension was also the most common adverse reaction leading to treatment discontinuation.

7 DRUG INTERACTIONS

7.1 Negative Inotropes and Chronotropes

Avoid concomitant use of RAPIBLYK with negative inotropes and medications that slow heart rate or cardiac conduction.

Beta-blockers, like RAPIBLYK, can cause depression of myocardial contractility and increase the risk of bradycardia or heart block. Concomitant use of RAPIBLYK with negative inotropes or chronotropes may augment these effects [see Warnings and Precautions (5.2)(5.3)].

7.2 Sympathomimetics, Positive Inotropes and Vasoconstrictors

Beta adrenergic agonists will antagonize the effects of RAPIBLYK and may attenuate the heart rate lowering effects of RAPIBLYK. Positive inotropes and vasoconstrictors may attenuate the heart rate and blood pressure lowering effects of RAPIBLYK.

7.3 Catecholamine Depleting Drugs

Observe patients treated with RAPIBLYK plus a catecholamine depletor (e.g., reserpine, monoamine oxidase inhibitors) for hypotension or marked bradycardia, which may cause vertigo, syncope, or postural hypotension.

Catecholamine depleting drugs may have an additive effect when given with beta-blockers, which may increase the risk of hypotension or marked bradycardia related vertigo, syncope, or postural hypotension [see Warnings and Precautions (5.1)].

8 USE IN SPECIFIC POPULATIONS

8.1 Pregnancy

Risk Summary

The available published data on RAPIBLYK use in pregnant women are insufficient to inform a drug associated risk of major birth defects, miscarriage or other adverse maternal or fetal outcomes. Landiolol exposure was limited to a single injection at the time of Cesarean delivery in a small clinical trial. Neonatal bradycardia, hypoglycemia, and respiratory depression have been observed with use of beta-blockers in pregnancy near the time of delivery (see Clinical Considerations). Administration of landiolol to pregnant rats showed distribution of landiolol to the placenta and the fetus. In animal reproduction studies, no embryo-fetal toxicity was observed in rats or rabbits during the period of organogenesis at landiolol exposure in rats approximately 2.7 times human exposure at the maximum recommended human dose (MRHD) (see Data).

The background risk of major birth defects and miscarriage for the indicated population is unknown. All pregnancies have a background risk of birth defect, loss, or other adverse outcomes. In the U.S. general population, the estimated background risk of major birth defects and miscarriage in clinically recognized pregnancies is 2% to 4% and 15% to 20%, respectively.

Clinical Considerations

Fetal/Neonatal Adverse Reactions

Landiolol crosses the placenta in rats. Neonates born to mothers who are receiving landiolol during pregnancy, may be at risk for hypotension, hypoglycemia, bradycardia, and respiratory depression. Monitor neonates exposed to landiolol during pregnancy and labor for hypotension, hypoglycemia, bradycardia, and respiratory depression and manage accordingly.

Data

Animal Data

Landiolol HCl was administered intravenously to pregnant rats (25, 50, or 100 mg/kg/day from gestation day 7 to 17) and rabbits (25, 50, or 100 mg/kg/day from gestation day 8 to 18). No adverse embryo-fetal effects were observed in rats at the landiolol HCl dose of 25 mg/kg/day, resulting in systemic landiolol exposure (AUC) of approximately 2.7-times the exposure at the MRHD. In rabbits, no adverse embryo-fetal effects were detected at the landiolol HCl dose of 100 mg/kg/day; the resulting systemic landiolol exposure (AUC) at this dose level was not determined.

In a prenatal and postnatal development study in rats, landiolol HCl was administered intravenously at 25, 50, or 100 mg/kg/day from gestation day 17 to postpartum/lactation day 20. A decrease in the viability index for the offspring on postpartum day 4 was observed for the high dose group. No effect on pre/post-natal development was observed at 50 mg/kg dose, which represents landiolol exposures approximately 5.4 times the human exposure at the MRHD.

8.2 Lactation

Risk Summary

There are no data on the presence of landiolol and its metabolites in human milk, the effects on the breastfed infant, or the effects on milk production. However, other drugs in this class are detected in human milk.

Landiolol was present in the milk of lactating rats (see Data). When a drug is present in animal milk, it is likely that the drug will be present in human milk, but the concentration of landiolol in animal milk does not necessarily predict the concentration of drug in human milk.

The developmental and health benefits of breastfeeding should be considered along with the mother’s clinical need for RAPIBLYK and any potential adverse effects on the breast fed infant from RAPIBLYK or from the underlying maternal condition.

Clinical Considerations

Monitoring for adverse reactions

Monitor the breastfed infant for bradycardia and other symptoms of beta blockade, such as lethargy (hypoglycemia).

Data

In a lactation study, administration of^14C-landiolol HCl administered as a single 1 mg/kg intravenous injection to lactating rats on postpartum/lactation day 13 to 14 was excreted in milk corresponding to approximately 70% of the concentration in plasma.

8.4 Pediatric Use

The safety and effectiveness of RAPIBLYK for the short-term reduction of ventricular rate in supraventricular tachycardia have been established in pediatric patients. Use of RAPIBLYK is supported by evidence from adequate and well-controlled studies in adults, with additional pharmacokinetic, pharmacodynamic and safety data from a descriptive single-arm, unblinded study that enrolled 60 pediatric patients from birth to <18 years of age. In this study, treatment with RAPIBLYK resulted in a >20% reduction in ventricular rate from baseline in patients with atrioventricular reentrant tachycardia (6/7, 85.7%), focal atrial tachycardia (4/8, 50%), junctional ectopic tachycardia (3/12, 25%), and in inappropriate sinus tachycardia (10/30, 33.3%) [see Clinical Pharmacology (12.3)].

8.5 Geriatric Use

Clinical studies of RAPIBLYK did not include sufficient numbers of subjects aged 65 and over to determine whether they respond differently from younger subjects. In general, dose selection for an elderly patient should usually start at the low end of the dosing range, reflecting greater frequency of decreased renal or cardiac function and of concomitant disease or other drug therapy.

8.6 Hepatic Impairment

More conservative dose titration is recommended in patients with mild hepatic impairment (Child-Pugh A). The effect of moderate or severe hepatic impairment (Child-Pugh B or C) on landiolol pharmacokinetics is unknown. Avoid use of RAPIBLYK in patients with moderate or severe hepatic impairment (Child-Pugh B or C). [see Pharmacokinetics (12.3)].

10 OVERDOSAGE

10.1 Signs and Symptoms of Overdose

Overdoses of RAPIBLYK injection can cause adverse cardiac and central nervous system effects. These adverse effects may precipitate severe signs, symptoms, sequelae, and complications such as severe cardiac and respiratory failure, including shock and coma, and may be fatal. Continuous monitoring of the patient is required.

- Cardiac adverse effects include bradycardia, atrioventricular block (1-, 2-, 3-degree), junctional rhythms, intraventricular conduction delays, decreased cardiac contractility, hypotension, cardiac failure (including cardiogenic shock), cardiac arrest/asystole, and pulseless electrical activity.
- Central nervous system adverse effects include respiratory depression, seizures, sleep and mood disturbances, fatigue, lethargy, and coma.
- In addition, bronchospasm, hyperkalemia, and hypoglycemia (especially in pediatric patients) may occur.

10.2 Treatment Recommendations

Because of its approximately 4-minute elimination half-life, the first step in the management of toxicity should be to discontinue RAPIBLYK infusion. Then, based on the observed clinical effects, consider the following general measures:

Bradycardia

Consider intravenous administration of atropine or another anticholinergic drug or cardiac pacing.

Cardiac Failure

Consider intravenous administration of a diuretic or digitalis glycoside. In shock resulting from inadequate cardiac contractility, consider intravenous administration of dopamine, dobutamine, isoproterenol, milrinone or inamrinone.

Symptomatic Hypotension

Consider intravenous administration of fluids or vasopressor agents such as dopamine or norepinephrine.

Bronchospasm

Consider intravenous administration of a beta agonist or a theophylline derivative.

11 DESCRIPTION

RAPIBLYK (landiolol) for injection is a beta-1 adrenergic receptor blocker with a very short duration of action (elimination half-life is approximately 4 minutes). Landiolol is:

- [(4S)-2,2-dimethyl-1,3-dioxolan-4-yl]methyl 3-[4-[(2S)-2-hydroxy-3-[2-(morpholine-4-carbonylamino)ethylamino]propoxy]phenyl]propionate and has the following structure:

- The active pharmaceutical ingredient is the hydrochloride salt of landiolol, which has the empirical formula C25H39N3O8 ∙ HCl and a molecular weight of 546.06 g/mol. It has two chiral centers and is used as pure S,S-enantiomer.
- Landiolol HCl is a white crystalline powder. It is a relatively hydrophilic compound, which is very soluble in water.

RAPIBLYK is supplied as a single presentation of 280 mg landiolol (equivalent to 300 mg landiolol HCl) as a white to almost white sterile lyophilized powder for intravenous injection in a single-dose vial. Inactive ingredients include 300 mg of mannitol and sodium hydroxide as needed to adjust pH.

12 CLINICAL PHARMACOLOGY

12.1 Mechanism of Action

RAPIBLYK is a selective beta-1-adrenoreceptor antagonist that inhibits the positive chronotropic effects of the catecholamines, epinephrine and norepinephrine, on the heart, where beta-1-receptors are predominantly located. Landiolol does not exhibit any membrane-stabilizing activity or intrinsic sympathomimetic activity at the approved recommend dosage in vitro.

12.2 Pharmacodynamics

Landiolol exposure-response relationships and the time course of pharmacodynamic response are not fully characterized.

12.3 Pharmacokinetics

Landiolol peak plasma concentration (Cmax) over the approved dosage range in healthy adult volunteers, patients with atrial fibrillation or atrial flutter and pediatric patients with supraventricular tachycardia is provided in Table 3.

Table 3: Landiolol peak plasma concentration (Cmax) in healthy volunteers and patients with atrial fibrillation or atrial flutter.

Landiolol Dosage | Peak Plasma Concentration (Cmax)
Landiolol Dosage | Healthy Adult Volunteers (mean)a | Adult Patients with Atrial Fibrillation or Atrial Flutter (range) | Pediatric Patients with Supraventricular Tachycardia (range)
9.3 mcg/kg/min | 0.2 mcg/mL | Not studied | Not available
18.6 mcg/kg/min | 0.5 mcg/mL | Not studied | Not available
37.3 mcg/kg/min | 1.0 mcg/mL | 0.52 to 1.77 mcg/mL | 0.52 to 4.71 mcg/mL

a 2 hour infusion

9.3 mcg/kg/min landiolol is equivalent to 10 mcg/kg/min landiolol hydrochloride.

Landiolol pharmacokinetics increases dose-proportionally in the dosage range of 9.3 to 74.6 mcg/kg/min (2 times the maximum approved recommended dosage). Landiolol reached steady-state values approximately 15 minutes after initiation of the infusion.

Distribution

Landiolol steady state volume of distribution is 0.4 L/kg. Landiolol protein binding is <10%.

Elimination

Landiolol elimination half-life is 4.5 minutes at steady state. Total body clearance of landiolol is 57 mL/kg/min following a 20-hour continuous landiolol infusion of 37.3 mcg/kg/min.

Metabolism

Landiolol is primarily metabolized by pseudocholinesterases and carboxylesterases in the plasma to the active metabolite M1.

M1 has less than 1/40th of the pharmacological activity of landiolol. M1 AUC0-inf is approximately 12 times greater than landiolol.

Excretion

Approximately 50 to 75% of the landiolol administered dose (approximately half of this as metabolite M1, and 8% as parent) is recovered in urine at 4 hours and 89 to 99% at 24 hours following a 60 min intravenous infusion.

Specific Populations

The effect of age and renal impairment on landiolol pharmacokinetics is unknown.

Patients with hepatic impairment

Landiolol geometric mean AUC increased by 44% and Cmax by 42% in 5 patients with mild hepatic impairment (Child-Pugh A) and 1 patient with moderate hepatic impairment (Child-Pugh B). The effect of moderate hepatic impairment (Child-Pugh B) on landiolol pharmacokinetics has not been fully characterized and the effect of severe hepatic impairment (Child-Pugh C) is unknown.

Drug Interaction Studies

In Vitro Studies

CYP 450 enzymes: Landiolol and the metabolite M1 are time-dependent CYP 2D6 inhibitors at exposures approximately 50 times the human exposure at the MRHD, but do not inhibit CYP 1A2, 2C9, 2C19, or 3A4.

13 NONCLINICAL TOXICOLOGY

13.1 Carcinogenesis, Mutagenesis, Impairment of Fertility

Carcinogenesis

Animal studies have not been conducted to evaluate the carcinogenic potential of RAPIBLYK.

Mutagenesis

Landiolol was not genotoxic when tested in a battery of assays (Ames, in vitro mouse lymphoma TK+/-, and in vivo micronucleus test in rats).

Impairment of Fertility

No adverse effects on fertility were observed in male and female rats administered a landiolol HCl dose of 100 mg/kg/day, resulting in systemic exposure (AUC) approximately 10-times the exposure at the MRHD

14 CLINICAL STUDIES

In 5 randomized, double-blind, placebo-controlled studies, treatment of 317 adults with supraventricular tachycardia with landiolol decreased heart rate in 40-90% of treated patients within about 10 minutes, compared to 0-11% of patients who received placebo; heart rate decrease was defined as a >20% decrease in heart rate or a heart rate <100 bpm or at least intermittent cessation of the arrhythmia. The infused dose of landiolol in these studies ranged from 9.3 to 74.6 mcg/kg/min (equivalent to 10 to 80 mcg/kg/min landiolol hydrochloride).

16 HOW SUPPLIED/STORAGE AND HANDLING

16.1 How Supplied

RAPIBLYK is supplied as a white to almost white, preservative-free, lyophilized powder in single dose vials containing 280 mg landiolol for injection (equivalent to 300 mg landiolol HCl).

Each vial is supplied in a carton NDC 87073-110-01

16.2 Storage

Store unreconstituted product at 20°C to 25°C (68ºF to 77ºF) [see USP Controlled Room Temperature], with excursions permitted to 15ºC to 30ºC (59ºF to 86ºF).